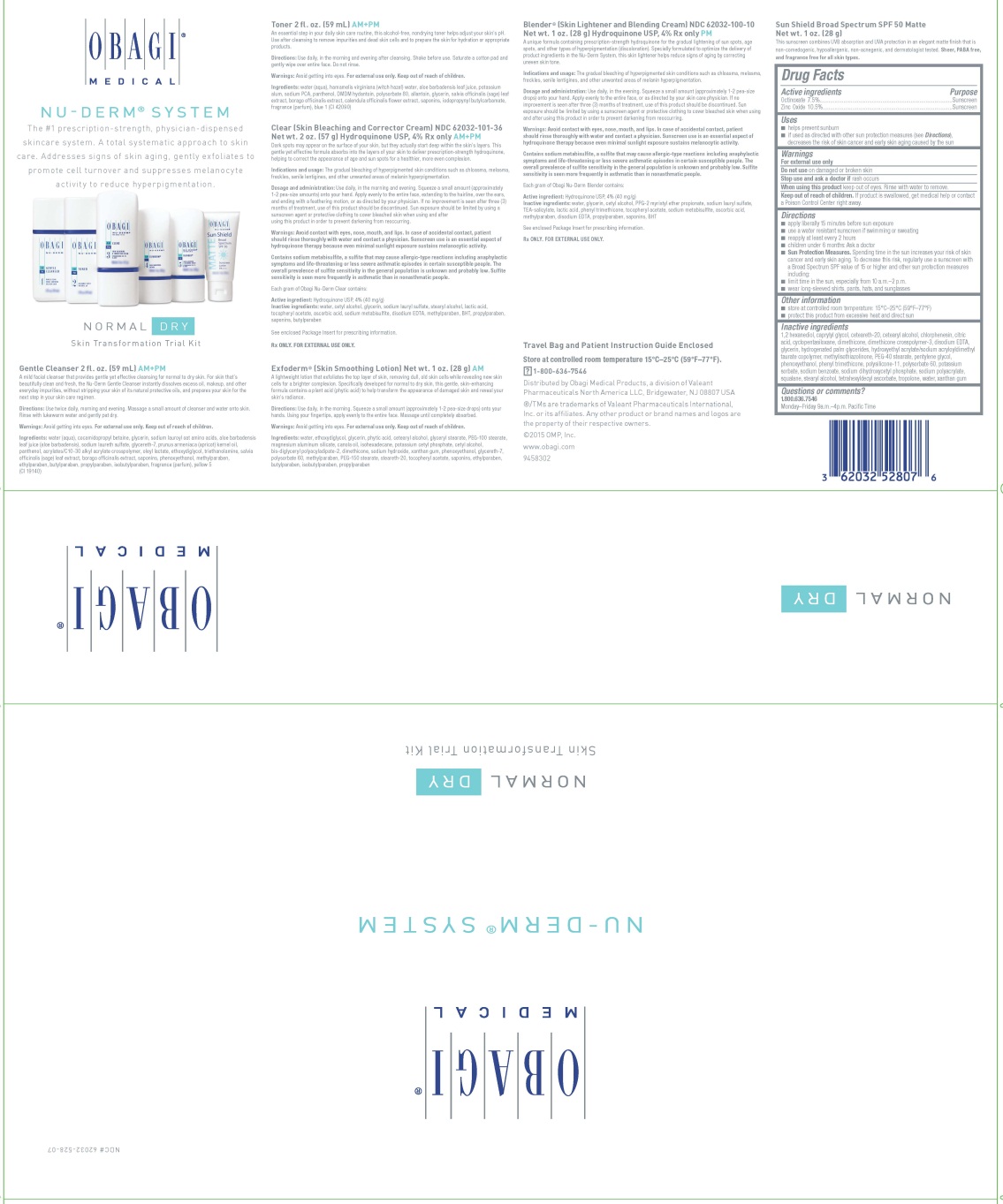 DRUG LABEL: Obagi Medical - Nu-Derm System - Normal to Dry - Skin Transformation Trial Kit
NDC: 62032-528 | Form: KIT | Route: TOPICAL
Manufacturer: Obagi Cosmeceuticals LLC
Category: otc | Type: HUMAN OTC DRUG LABEL
Date: 20191113

ACTIVE INGREDIENTS: OCTINOXATE 75 mg/1 g; ZINC OXIDE 105 mg/1 g; HYDROQUINONE 40 mg/1 g; HYDROQUINONE 40 mg/1 g
INACTIVE INGREDIENTS: 1,2-HEXANEDIOL; CAPRYLYL GLYCOL; POLYOXYL 20 CETOSTEARYL ETHER; CETOSTEARYL ALCOHOL; CHLORPHENESIN; CITRIC ACID MONOHYDRATE; CYCLOMETHICONE 5; DIMETHICONE; EDETATE DISODIUM; GLYCERIN; HYDROGENATED PALM GLYCERIDES; HYDROXYETHYL ACRYLATE/SODIUM ACRYLOYLDIMETHYL TAURATE COPOLYMER (45000 MPA.S AT 1%); METHYLISOTHIAZOLINONE; PEG-40 STEARATE; PENTYLENE GLYCOL; PHENOXYETHANOL; PHENYL TRIMETHICONE; POLYSORBATE 60; POTASSIUM SORBATE; SODIUM BENZOATE; SODIUM DIHYDROXYCETYL PHOSPHATE; SQUALANE; STEARYL ALCOHOL; TETRAHEXYLDECYL ASCORBATE; TROPOLONE; WATER; XANTHAN GUM; WATER; CETYL ALCOHOL; GLYCERIN; SODIUM LAURYL SULFATE; STEARYL ALCOHOL; LACTIC ACID; .ALPHA.-TOCOPHEROL ACETATE; ASCORBIC ACID; SODIUM METABISULFITE; EDETATE DISODIUM; METHYLPARABEN; BUTYLATED HYDROXYTOLUENE; PROPYLPARABEN; BUTYLPARABEN; WATER; GLYCERIN; CETYL ALCOHOL; PPG-2 MYRISTYL ETHER PROPIONATE; SODIUM LAURYL SULFATE; TROLAMINE SALICYLATE; LACTIC ACID; PHENYL TRIMETHICONE; .ALPHA.-TOCOPHEROL ACETATE; SODIUM METABISULFITE; ASCORBIC ACID; METHYLPARABEN; EDETATE DISODIUM; PROPYLPARABEN; BUTYLATED HYDROXYTOLUENE

OBAGI MEDICAL
NU-DERM® SYSTEM
NORMAL to DRY
Skin Transformation Trial Kit

Gentle Cleanser AM+PM

A mild facial cleanser that provides gentle yet effective cleansing for normal to dry skin. For skin that's beautifully clean and fresh, the Gentle Cleanser instantly dissolves excess oil, makeup, and other everyday impurities, without stripping your skin of its natural protective oils, and prepares your skin for the next step in your skin care regimen.

Directions

Use twice daily, morning and evening. Massage a small amount of cleanser and water onto skin. Rinse with lukewarm water and gently pat dry.

Warnings

Avoid getting into eyes. For external use only. Keep out of reach of children.

Ingredients

water (aqua), cocamidopropyl betaine, glycerin, sodium lauroyl oat amino acids, aloe barbadensis leaf juice (aloe barbadensis), sodium laureth sulfate, glycereth-7, prunus armeniaca (apricot) kernel oil, panthenol, acrylates/C10-30 alkyl acrylate crosspolymer, oleyl lactate, ethoxydiglycol, triethanolamine, salvia officinalis (sage) leaf extract, borago officinalis extract, saponins, phenoxyethanol, methylparaben, ethylparaben, butylparaben, propylparaben, isobutylparaben, fragrance (parfum), yellow 5 (CI 19140)

Toner AM+PM

An essential step in your daily skin care routine, this alcohol-free, nondrying toner helps adjust your skin's pH. Use after cleansing to remove impurities and dead skin cells and to prepare the skin for hydration or appropriate products.

Directions

Use daily, in the morning and evening after cleansing. Shake before use. Saturate a cotton pad and gently wipe over the entire face. Do not rinse.

Warnings

Avoid getting into eyes. For external use only. Keep out of reach of children.

Ingredients

water (aqua), hamamelis virginiana (witch hazel) water, aloe barbadensis leaf juice, potassium alum, sodium PCA, panthenol, DMDM hydantoin, polysorbate 80, allantoin, glycerin, salvia officinalis (sage) leaf extract, borago officinalis extract, calendula officinalis flower extract, saponins, iodopropynyl butylcarbamate, fragrance (parfum), blue 1 (CI 42090)

Clear (Skin Bleaching and Corrector Cream) AM+PM

Dark spots may appear on the surface of your skin, but they actually start deep within the skin's layers. This gentle yet effective formula absorbs into the layers of your skin to deliver prescription-strength hydroquinone, helping to correct the appearance of age and sun spots for a healthier, more even complexion.

Indications and Usage

The gradual bleaching of hyperpigmented skin conditions such as chloasma, melasma, freckles, senile lentigines, and other unwanted areas of melanin hyperpigmentation.

Dosage and Administration

Use daily, in the morning and evening. Squeeze a small amount (approximately1-2 pea-size amounts) onto your hand. Apply evenly to the entire face, extending to the hairline, over the ears, and ending with a feathering motion, or as directed by your physician. If no improvement is seen after three (3) months of treatment, use of this product should be discontinued. Sun exposure should be limited by using a sunscreen agent or protective clothing to cover bleached skin when using and after using this product in order to prevent darkening from reoccurring.

Warnings

Avoid contact with eyes, nose, mouth, and lips. In case of accidental contact, patient should rinse thoroughly with water and contact a physician. Sunscreen use is an essential aspect of hydroquinone therapy because even minimal sunlight exposure sustains melanocytic activity.

Contains sodium metabisulfite, a sulfite that may cause allergic-type reactions including anaphylactic symptoms and life-threatening or less severe asthmatic episodes in certain susceptible people. The overall prevalence of sulfite sensitivity in the general population is unknown and probably low. Sulfite sensitivity is seen more frequently in asthmatic than in nonasthmatic people.

Each gram of Obagi Nu-Derm Blender contains:

Active Ingredient

Hydroquinone USP, 4% (40 mg/g)

Inactive Ingredients

water, cetyl alcohol, glycerin, sodium lauryl sulfate, stearyl alcohol, lactic acid, tocopheryl acetate, ascorbic acid, sodium metabisulfite, disodium EDTA, methylparaben, BHT, propylparaben, saponins, butylparaben

See enclosed Package Insert for prescribing information.

Rx ONLY. FOR EXTERNAL USE ONLY.

Exfoderm® (Skin Smoothing Lotion) AM

A lightweight lotion that exfoliates the top layer of skin, removing dull, old skin cells while revealing new skin cells for a brighter complexion. Specifically developed for normal to dry skin, this gentle, skin-enhancing formula contains a plant acid (phytic acid) to help transform the appearance of damaged skin and reveal your skin's radiance.

Directions

Use daily, in the morning. Squeeze a small amount (approximately 1 to 2 pea-size drops) onto your hands. Using your fingertips, apply evenly to the entire face. Massage until completely absorbed.

Warnings

Avoid getting into eyes. For external use only. Keep out of reach of children.

Ingredients

water, ethoxydiglycol, glycerin, phytic acid, cetearyl alcohol, glyceryl stearate, PEG-100 stearate, magnesium aluminum silicate, canola oil, isohexadecane, potassium cetyl phosphate, cetyl alcohol, bis-diglyceryl polyacyladipate-2, dimethicone, sodium hydroxide, xanthan gum, phenoxyethanol, glycereth-7, polysorbate 60, methylparaben, PEG-150 stearate, steareth-20, tocopheryl acetate, saponins, ethylparaben, butylparaben, isobutylparaben, propylparaben

Blender® (Skin Lightener and Blending Cream) PM

A unique formula containing prescription-strength hydroquinone for the gradual lightening of sun spots, age spots, and other types of hyperpigmentation (discoloration). Specially formulated to optimize the delivery of product ingredients in the Nu-Derm System, this skin lightener helps reduce signs of aging by correcting uneven skin tone.

Indications and Usage

The gradual bleaching of hyperpigmented skin conditions such as chloasma, melasma, freckles, senile lentigines, and other unwanted areas of melanin hyperpigmentation.

Dosage and Administration

Use daily, in the evening. Squeeze a small amount (approximately 1-2 pea-size drops) onto your hand. Apply evenly to the entire face, or as directed by your skin care physician. If no improvement is seen after three (3) months of treatment, use of this product should be discontinued. Sun exposure should be limited by using a sunscreen agent or protective clothing to cover bleached skin when using and after using this product in order to prevent darkening from reoccurring.

Warnings

Avoid contact with eyes, nose, mouth, and lips. In case of accidental contact, patient should rinse thoroughly with water and contact a physician. Sunscreen use is an essential aspect of hydroquinone therapy because even minimal sunlight exposure sustains melanocytic activity.

Contains sodium metabisulfite, a sulfite that may cause allergic-type reactions including anaphylactic symptoms and life-threatening or less severe asthmatic episodes in certain susceptible people. The overall prevalence of sulfite sensitivity in the general population is unknown and probably low. Sulfite sensitivity is seen more frequently in asthmatic than in nonasthmatic people.

Each gram of Obagi Nu-Derm Blender contains:

Active Ingredient

Hydroquinone USP, 4% (40 mg/g)

Inactive Ingredients

water, glycerin, cetyl alcohol, PPG-2 myristyl ether propionate, sodium lauryl sulfate, TEA-salicylate, lactic acid, phenyl trimethicone, tocopheryl acetate, sodium metabisulfite, ascorbic acid, methylparaben, disodium EDTA, propylparaben, saponins, BHT

See enclosed Package Insert for prescribing information.

Rx ONLY. FOR EXTERNAL USE ONLY

Sun Shield Broad Spectrum SPF 50 Matte

Drug Facts

Active ingredients

Octinoxate 7.5%

Zinc Oxide 10.5%

Purpose

Sunscreen

Uses

- helps prevent sunburn
- if used as directed with other sun protection measures (see Directions), decreases the risk of skin cancer and early skin aging caused by the sun

Warnings

For external use only

Do not use on damaged or broken skin

Stop use and ask a doctor if rash occurs

When using this product keep out of eyes. Rinse with water to remove.

Keep Out of Reach of Children

If swallowed, get medical help or contact a Poison Control Center right away.

Directions

- apply liberally 15 minutes before sun exposure
- use a water resistant sunscreen if swimming or sweating
- reapply at least every 2 hours
- children under 6 months: Ask a doctor
- Sun Protection Measures. Spending time in the sun increases your risk of skin cancer and early skin aging. To decrease this risk, regularly use a sunscreen with a Broad Spectrum SPF value of 15 or higher and other sun protection measures including:
  - limit time in the sun, especially from 10 a.m.–2 p.m.
  - wear long-sleeved shirts, pants, hats, and sunglasses

Other information

- store at controlled room temperature: 15°C–25°C (59°F–77°F)
- protect this product from excessive heat and direct sun

Inactive ingredients

1,2 hexanediol, caprylyl glycol, ceteareth-20, cetearyl alcohol, chlorphenesin, citric acid, cyclopentasiloxane, dimethicone, dimethicone crosspolymer-3, disodium EDTA, glycerin, hydrogenated palm glycerides, hydroxyethyl acrylate/sodium acryloyldimethyl taurate copolymer, methylisothiazolinone, PEG-40 stearate, pentylene glycol, phenoxyethanol, phenyl trimethicone, polysilicone-11, polysorbate 60, potassium sorbate, sodium benzoate, sodium dihydroxycetyl phosphate, sodium polyacrylate, squalane, stearyl alcohol, tetrahexyldecyl ascorbate, tropolone, water, xanthan gum

Questions or comments?

1.800.636.7546
Monday–Friday 9 a.m.–4 p.m. Pacific Time

Principal Display Panel - Kit Carton

OBAGI®

MEDICAL

OBAGI NU-DERM® SYSTEM

NORMAL DRY

Skin Transformation Trial Kit